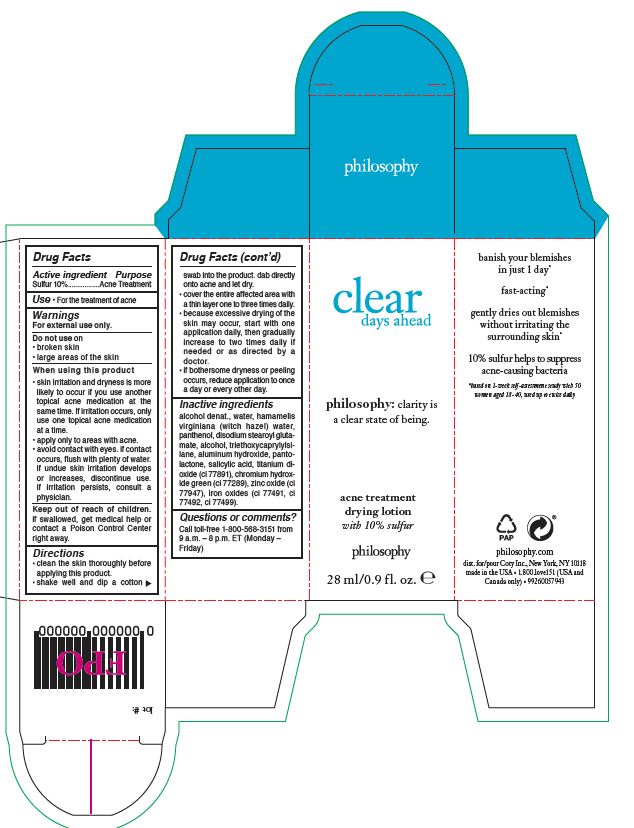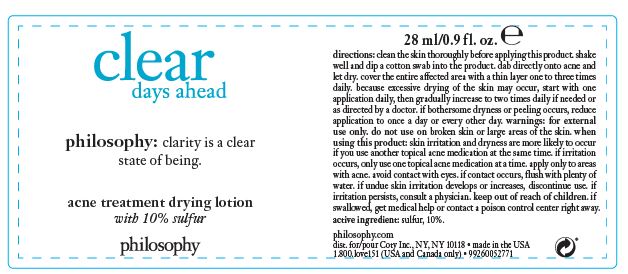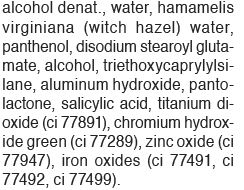 DRUG LABEL: Philosophy Clear Days Ahead Acne Treatment
NDC: 50184-1067 | Form: LOTION
Manufacturer: Philosophy, Inc.
Category: otc | Type: HUMAN OTC DRUG LABEL
Date: 20230124

ACTIVE INGREDIENTS: SULFUR 10 g/100 mL
INACTIVE INGREDIENTS: WATER; TITANIUM DIOXIDE; CHROMIUM HYDROXIDE GREEN; FERROSOFERRIC OXIDE; ALCOHOL; TRIETHOXYCAPRYLYLSILANE; PANTOLACTONE, (R)-; SALICYLIC ACID; PANTHENOL; ALUMINUM HYDROXIDE; ZINC OXIDE; DISODIUM STEAROYL GLUTAMATE; FERRIC OXIDE RED; HAMAMELIS VIRGINIANA TOP WATER

Philosophy Clear Days Ahead Acne Treatment Drying Lotion

Active ingredient

Sulfur 10%

Purpose

Acne Treatment

Use

For the treatment of acne.

Warnings

For external use only.

Do not use

- broken skin
- large areas of the skin

When using this product

- skin irritation and dryness is more likely to occur if you use another topical acne medication at the same time. If irritation occurs, only use one topical acne medication at a time.
- apply only to areas with acne.
- avoid contact with eyes. if contact occurs, flush with plenty of water. if undue skin irritation develops or increases, discontiue use. if irritation persists, consult a physician.

keep out of reach of children

if swallowed, get medical help or contact Poison Control Center right away.

Directions

- clean the skin thoroughly before applying this product.
- shake well and dip a cotton swab into the product. dab directly onto acne and let dry.
- cover the entire affected area with a thin layer one to three times daily.
- because excessive drying of the skin may occur, start with one application daily, then gradually increase to two times daily if needed or as directed by a doctor.
- if bothersome dryness or peeling occurs, reduce application to once a day or every other day.

Questions or Comments?

Call toll-free 1-800-568-3151 from 9 a.m. – 8 p.m. ET (Monday –Friday)

PACKAGE LABEL

clear

days ahead

philosophy: clarity is

a clear state of being.

acne treatment

drying lotion

with 10% sulfur

philosophy

28 ml/0.9 fl. oz. e